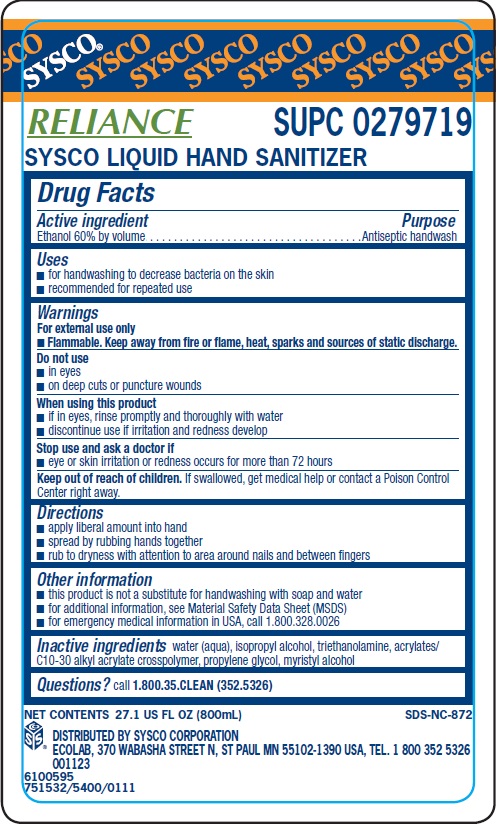 DRUG LABEL: Sysco Reliance
NDC: 47593-480 | Form: SOLUTION
Manufacturer: Ecolab Inc.
Category: otc | Type: HUMAN OTC DRUG LABEL
Date: 20240426

ACTIVE INGREDIENTS: ALCOHOL 60 mL/100 mL
INACTIVE INGREDIENTS: WATER; ISOPROPYL ALCOHOL; TROLAMINE; CARBOMER COPOLYMER TYPE B (ALLYL PENTAERYTHRITOL CROSSLINKED); PROPYLENE GLYCOL; MYRISTYL ALCOHOL

Drug Facts

Active ingredient

Ethanol 60% by volume

Purpose

Antiseptic handwash

Uses

- for handwashing to decrease bacteria on the skin
- recommended for repeated use

Warnings

For external use

- Flammable. Keep away from fire or flame, heat, sparks and sources of static discharge.

Do not use

- in eyes
- on deep cuts or puncture wounds

When using this product

- if in eyes, rinse promptly and thoroughly with water
- discontinue use if irritation and redness develop

Stop use and ask a doctor if

- eye or skin irritation or redness occurs for more than 72 hours

KEEP OUT OF REACH OF CHILDREN

Keep our of reach of children. If swallowed, get medical help or contact a Poison Control Center right away.

Directions

- apply liberal amount into hand
- spread by rubbing hands together
- rub to dryness with attention to area around nails and between fingers

Other information

- this product is not a substitute for handwashing with soap and water
- for additional information, see Material Safety Data Sheet (MSDS)
- for emergency medical information in USA, call 1.800.328.0026

INACTIVE INGREDIENT

Inactive ingredients water (aqua), isopropyl alcohol, triethanolamine, acrylates/C10-30 alkyl acrylate crosspolymer, propylene glycol, myristyl alcohol

Questions? call 1.800.35.CLEAN (352.5326)

Principal display panel and representative label

SYSCO

RELIANCE SUPC 0279719

SYSCO LIQUID HAND SANITIZER

NET CONTENTS 27.1 US FL OZ (800mL) SDS-NC-872

DISTRIBUTED BY SYSCO CORPORATION

ECOLAB, 370 WABASHA STREET N, ST PAUL MN 55102-1390 USA, TEL. 1 800 352 5326

001123

6100595

751532/5400/0111